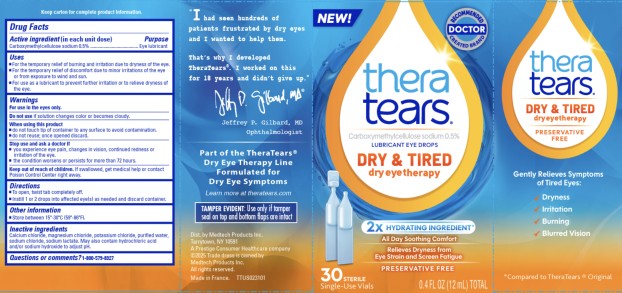 DRUG LABEL: TheraTears Dry and Tired
NDC: 58790-013 | Form: SOLUTION/ DROPS
Manufacturer: MEDTECH PRODUCTS INC
Category: otc | Type: HUMAN OTC DRUG LABEL
Date: 20260107

ACTIVE INGREDIENTS: CARBOXYMETHYLCELLULOSE SODIUM 5 mg/1 mL
INACTIVE INGREDIENTS: CALCIUM CHLORIDE; MAGNESIUM CHLORIDE; POTASSIUM CHLORIDE; WATER; SODIUM CHLORIDE; SODIUM LACTATE; HYDROCHLORIC ACID; SODIUM HYDROXIDE

TheraTears Dry and Tired Dry Eye Therapy PF - 58790-013

THERATEARS LUBRICANT- carboxymethylcellulose sodium solution/ drops
Medtech Products Inc., a Prestige Consumer Healthcare company

Disclaimer: Most OTC drugs are not reviewed and approved by FDA, however they may be marketed if they comply with applicable regulations and policies. FDA has not evaluated whether this product complies.

----------

Drug Facts

Active ingredient (In each unit dose)

Sodium Carboxymethylcellulose 0.5%

Purpose

Eye lubricant

Uses

- For the temporary relief of burning and irritation due to dryness of the eye.
- For the temporary relief of discomfort due to minor irritations of the eye or from exposure to wind and sun.
- For use as a lubricant to prevent further irritation or to relieve dryness of the eye.

Warnings

For use in the eyes only.

Do not use

if solution changes color or becomes cloudy.

When using this product

■ do not touch tip of container to any surface to avoid contamination.

■ do not reuse; once opened discard.

Stop use and ask a doctor if

■ you experience eye pain, changes in vision, continued redness or irritation of the eye.

■ the condition worsens or persists for more than 72 hours.

Keep out of reach of children.

If swallowed, get medical help or contact a Poison Control Center right away.

Directions

- To open, twist tab completely off.
- Instill 1 or 2 drops into affected eye(s) as needed and discard container.

Other information

- Store between 15º-30ºC (59º-86ºF).

Inactive ingredients

Calcium chloride, magnesium chloride, potassium chloride, purified water, sodium chloride, sodium lactate. May also contain hydrochloric acid and/or sodium hydroxide to adjust pH.

Questions and comments?

1-800-579-8327

Principal Display Panel

Carboxymethylcellulose sodium 0.5%

LUBRICANT EYE DROPS

DRY & TIRED

dry eye therapy

PRESERVATIVE FREE

30 STERILE

Single-Use Vials

0.4 FL OZ (12 mL) TOTAL